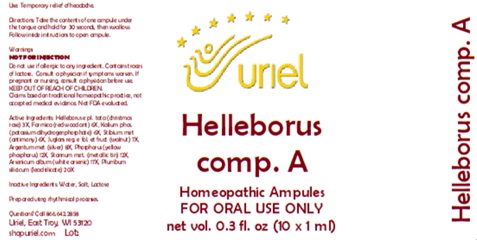 DRUG LABEL: Helleborus comp. A
NDC: 48951-5135 | Form: LIQUID
Manufacturer: Uriel Pharmacy Inc.
Category: homeopathic | Type: HUMAN OTC DRUG LABEL
Date: 20251121

ACTIVE INGREDIENTS: TIN 12 [hp_X]/1 mL; PHOSPHORUS 12 [hp_X]/1 mL; ARSENIC TRIOXIDE 17 [hp_X]/1 mL; LEAD MONOSILICATE 20 [hp_X]/1 mL; SILVER 8 [hp_X]/1 mL; FORMICA RUFA 6 [hp_X]/1 mL; ANTIMONY 6 [hp_X]/1 mL; HELLEBORUS NIGER ROOT 3 [hp_X]/1 mL; POTASSIUM PHOSPHATE, MONOBASIC 6 [hp_X]/1 mL; JUGLANS REGIA LEAF 7 [hp_X]/1 mL
INACTIVE INGREDIENTS: WATER; SODIUM CHLORIDE; LACTOSE, UNSPECIFIED FORM

Helleborus comp. A

PURPOSE

Use: Temporary relief of headache.

INDICATIONS AND USAGE

FOR ORAL USE ONLY

DOSAGE AND ADMINISTRATION

Directions: Take the contents of one ampule under
the tongue and hold for 30 seconds, then swallow.
Follow inside instructions to open ampule.

Warnings:
NOT FOR INJECTION
Do not use if allergic to any ingredient. Contains traces of lactose. Consult a physician if symptoms worsen. If pregnant or nursing, consult a physician before use.

Claims based on traditional homeopathic practice, not accepted medical evidence. Not FDA evaluated.

KEEP OUT OF REACH OF CHILDREN.

ACTIVE INGREDIENT

Active Ingredients: Helleborus (Christmas rose) 3X, Formica (Red wood ant) 6X, Kalium phos.(potassium dihydrogenphosphate) 6X,Stibium met. (Antimony) 6X, Juglans reg. e fol. et fruct (walnut) 7X, Argentum met. (Silver) 8X, Phosphorus (Yellow phosphorus) 12X, Arsenicum (White arsenic) 17X, Plumbum silicicum (Lead silicate) 20X

Inactive Ingredients: Water, Salt, Lactose

Prepared using rhythmical processes.

Questions? Call 866.642.2858
Uriel, East Troy, WI 53120
shopuriel.com Lot: